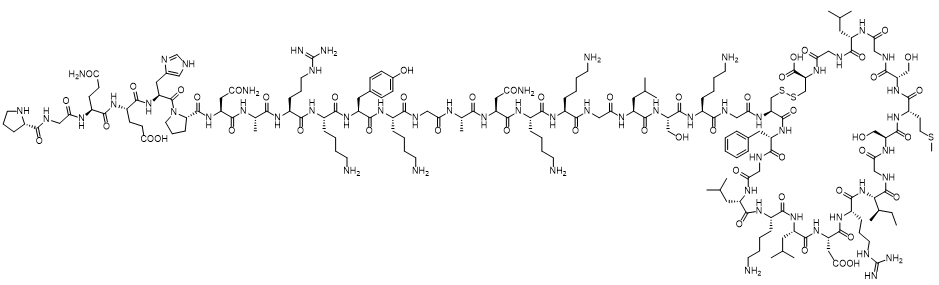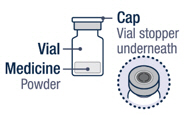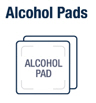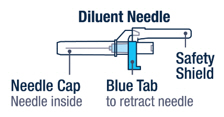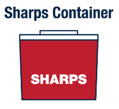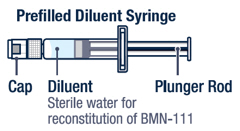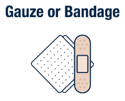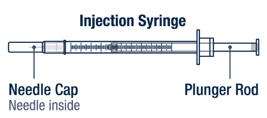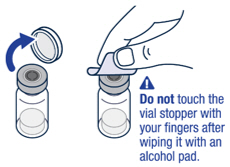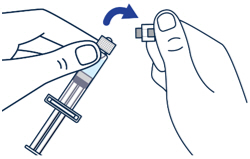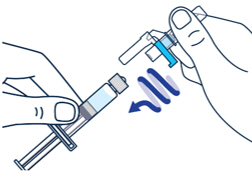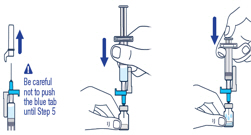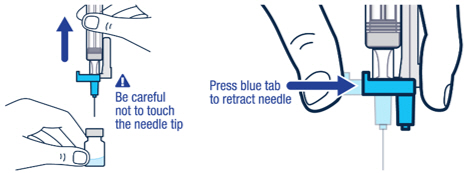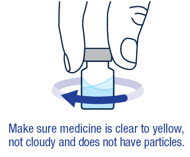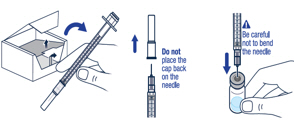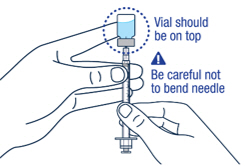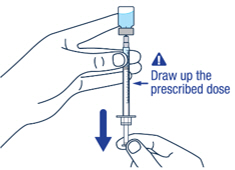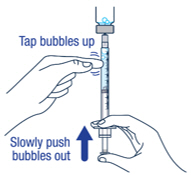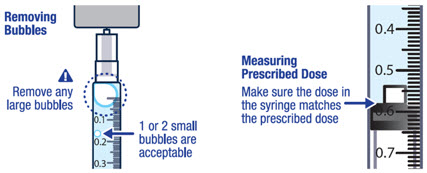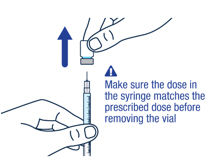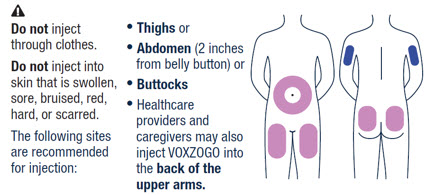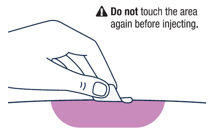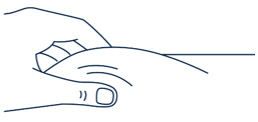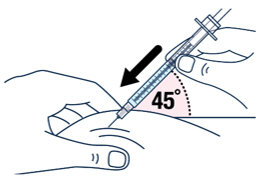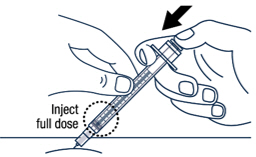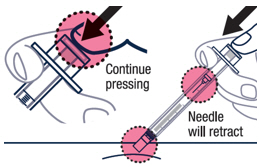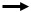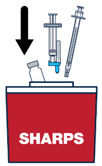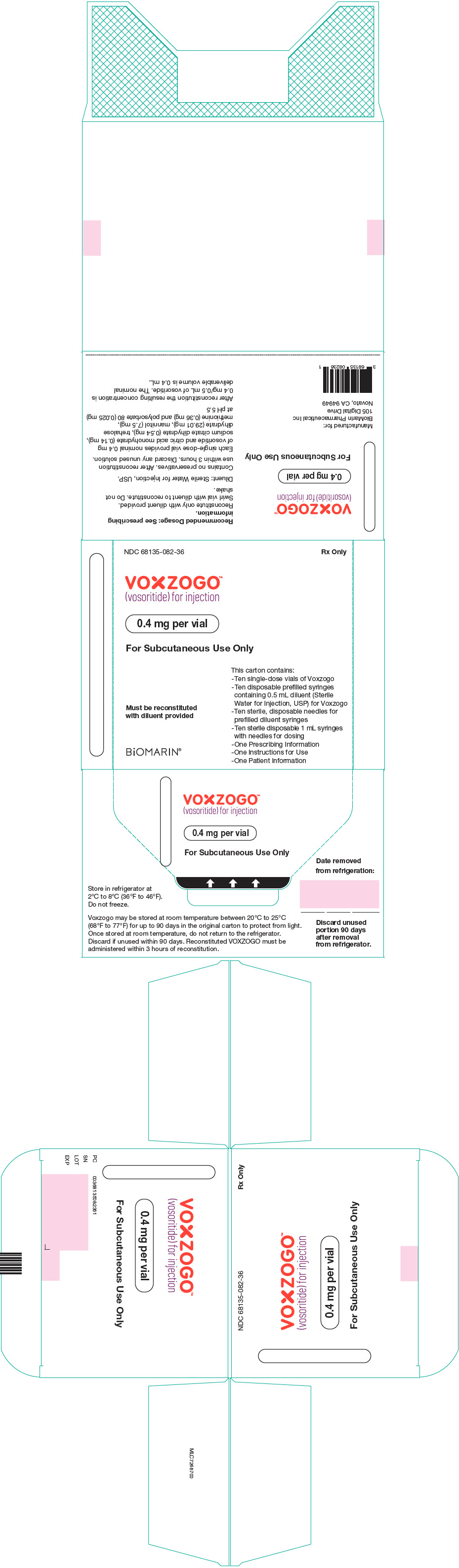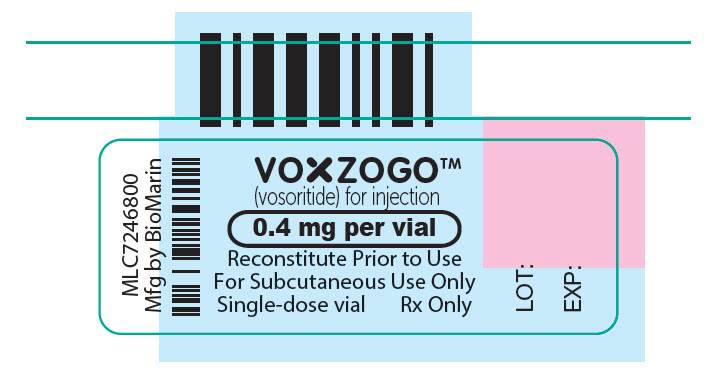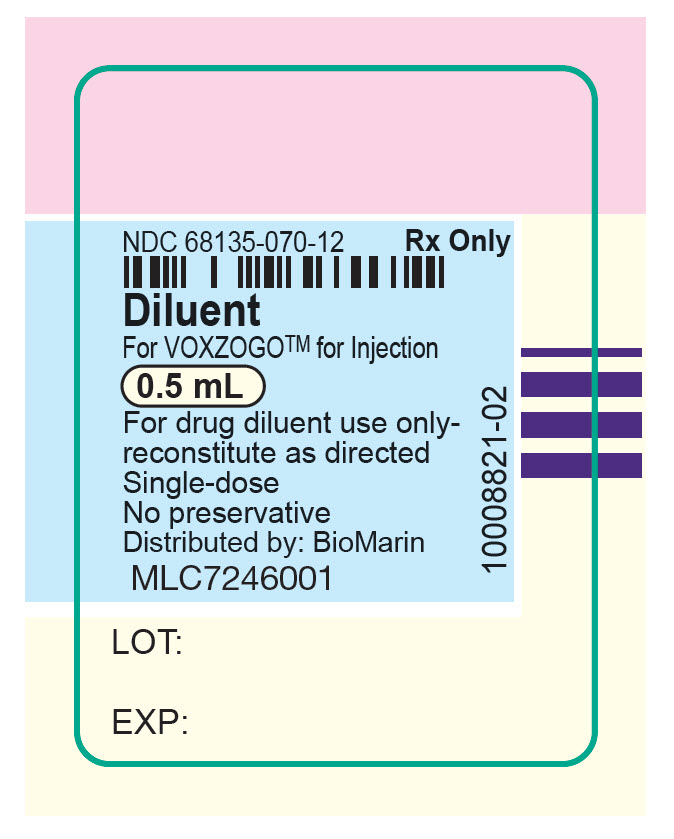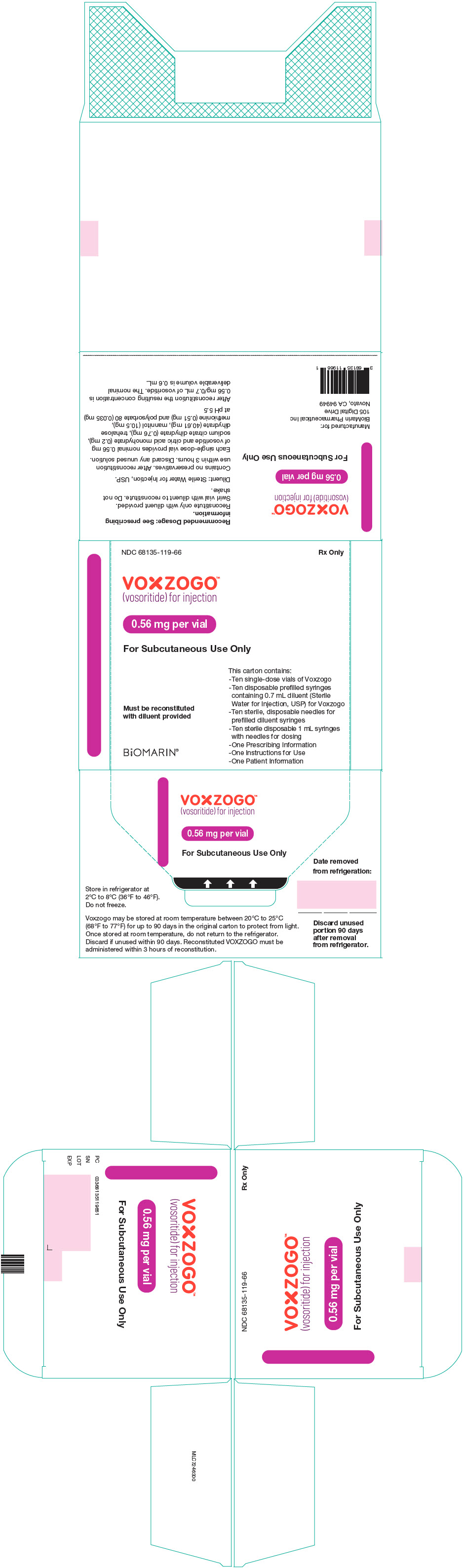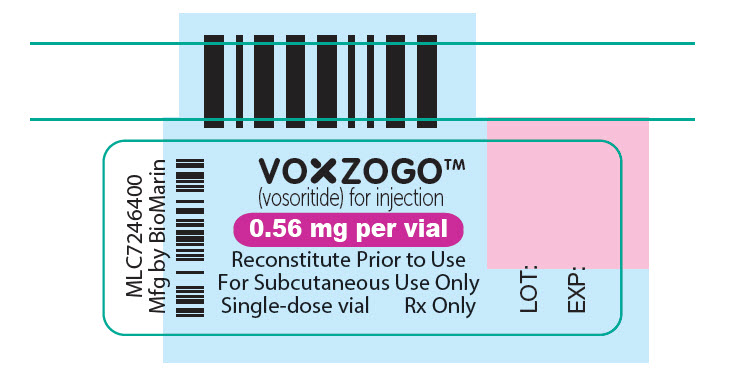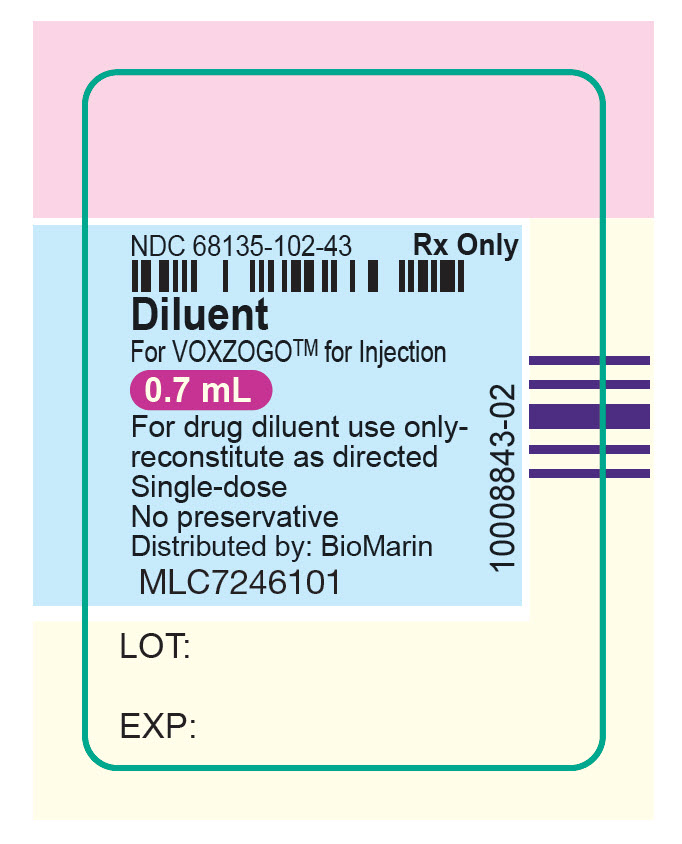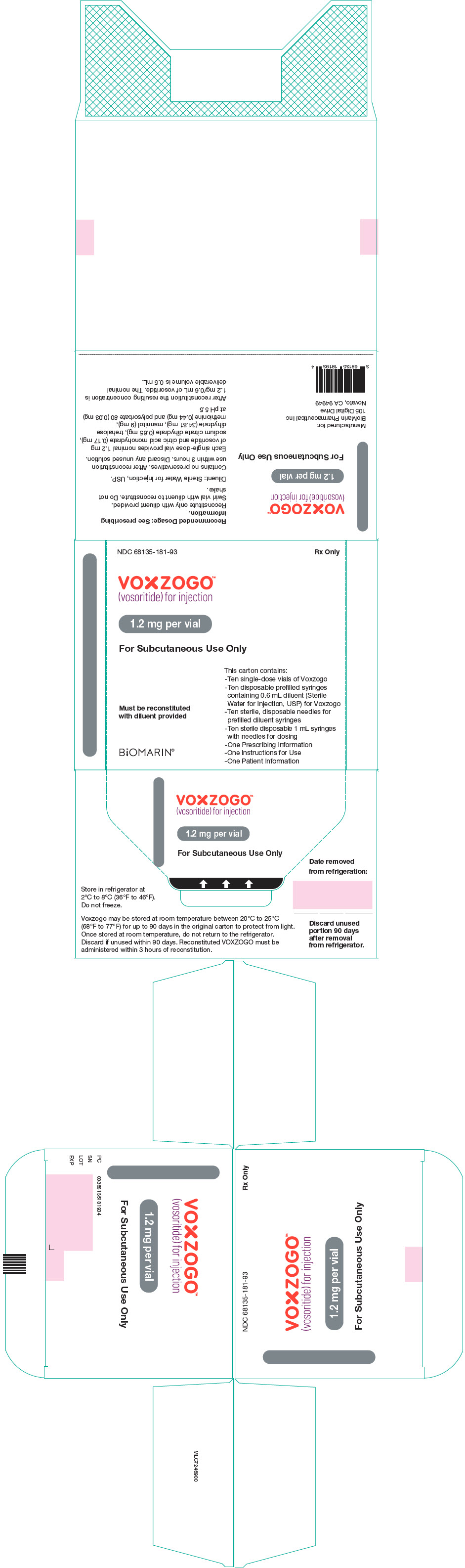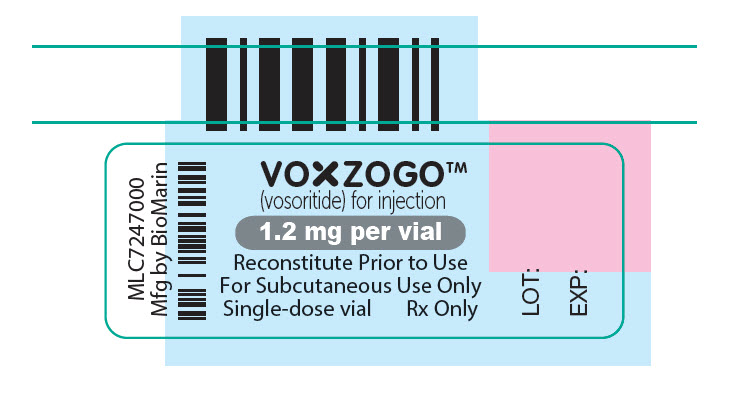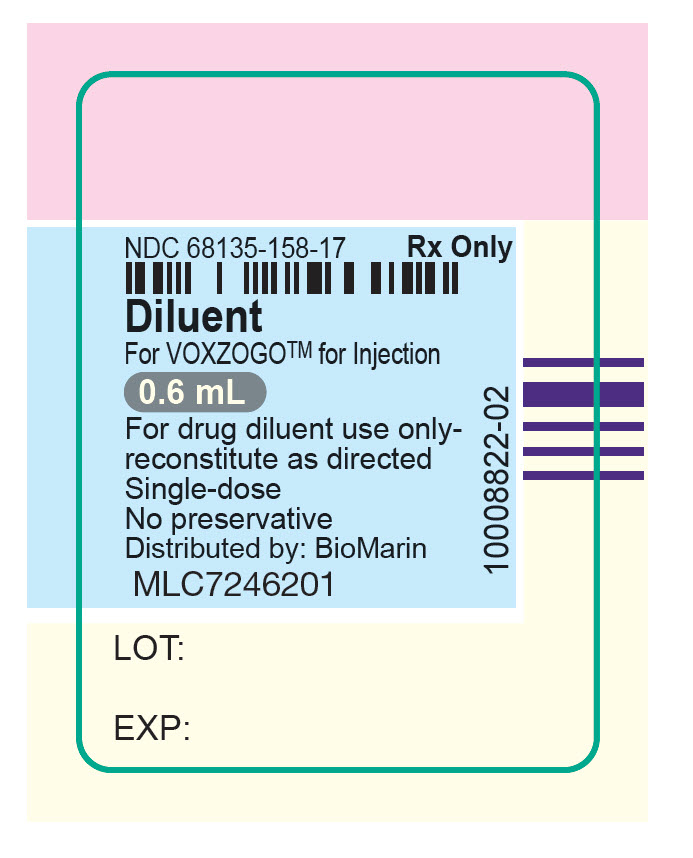 DRUG LABEL: VOXZOGO 0.4mg
NDC: 68135-082 | Form: KIT | Route: SUBCUTANEOUS
Manufacturer: BioMarin Pharmaceutical Inc.
Category: prescription | Type: HUMAN PRESCRIPTION DRUG LABEL
Date: 20251125

ACTIVE INGREDIENTS: VOSORITIDE 0.4 mg/0.5 mL

HIGHLIGHTS OF PRESCRIBING INFORMATION

These highlights do not include all the information needed to use VOXZOGO safely and effectively. See full prescribing information for VOXZOGO.
VOXZOGO (vosoritide) for injection, for subcutaneous use
Initial U.S. Approval: 2021

1 INDICATIONS AND USAGE

VOXZOGO is a C type natriuretic peptide (CNP) analog indicated to increase linear growth in pediatric patients with achondroplasia with open epiphyses. This indication is approved under accelerated approval based on an improvement in annualized growth velocity. Continued approval for this indication may be contingent upon verification and description of clinical benefit in confirmatory trial(s). (1)

2 DOSAGE AND ADMINISTRATION

- Ensure adequate food and fluid intake prior to administration. (2.1)
- Recommended dosage is based on patient's actual body weight. Administer VOXZOGO subcutaneously once daily. (2.2)
- Reconstitute prior to use. Injection volume is based on both patient's weight and concentration of reconstituted VOXZOGO. (2.2)
- Monitor growth and adjust dosage according to actual body weight. Permanently discontinue upon closure of epiphyses. (2.3)
- See full prescribing information for reconstitution, dilution, and administration instructions. (2.4)

3 DOSAGE FORMS AND STRENGTHS

For injection: 0.4 mg, 0.56 mg, or 1.2 mg of vosoritide as a lyophilized powder in a single-dose vial for reconstitution. (3)

4 CONTRAINDICATIONS

None. (4)

5 WARNINGS AND PRECAUTIONS

Risk of Low Blood Pressure: Transient decreases in blood pressure have been reported. Instruct patients to be well-hydrated and have adequate food intake prior to administration of VOXZOGO (5.1)

6 ADVERSE REACTIONS

Most common adverse reactions (>10%) are injection site erythema, injection site swelling, rash, vomiting, injection site urticaria, arthralgia, decreased blood pressure, and gastroenteritis. (6.1)

To report SUSPECTED ADVERSE REACTIONS, contact BioMarin Pharmaceutical Inc. at 1-866-906-6100, or FDA at 1-800-FDA-1088 or www.fda.gov/medwatch.

8 USE IN SPECIFIC POPULATIONS

Renal Impairment: Not recommended in patients with eGFR < 60 mL/min/1.73 m^2. (8.6)

FULL PRESCRIBING INFORMATION

1 INDICATIONS AND USAGE

VOXZOGO is indicated to increase linear growth in pediatric patients with achondroplasia with open epiphyses. This indication is approved under accelerated approval based on an improvement in annualized growth velocity [see Clinical Studies (14)]. Continued approval for this indication may be contingent upon verification and description of clinical benefit in confirmatory trial(s).

2 DOSAGE AND ADMINISTRATION

2.1 Important Instructions Prior to Administration of VOXZOGO

To reduce the risk of low blood pressure and its associated signs and symptoms, instruct the caregiver and patient that the patient should [see Warnings and Precautions (5.1)]:

- Have adequate food intake prior to VOXZOGO administration.
- Drink approximately 240 to 300 mL of fluid in the hour prior to VOXZOGO administration.

2.2 Recommended Dosage and Administration

The recommended dosage of VOXZOGO is based on the patient's actual body weight (see Table 1). VOXZOGO is administered by subcutaneous injection once daily [see Dosage and Administration (2.4)].

Inject VOXZOGO at approximately the same time each day, if possible. The volume of VOXZOGO to be administered (injection volume) is based on the patient's actual body weight and the concentration of reconstituted VOXZOGO (0.8 mg/mL or 2 mg/mL) (see Table 1). VOXZOGO must be reconstituted prior to use [see Dosage and Administration (2.4)].

Table 1: Recommended VOXZOGO Daily Dosage and Injection Volume
Actual Body Weight [Intermediate body weights that fall within these weight bands should be rounded to the nearest whole number.] | Dose | Injection Volume | Vial Strength for Reconstitution [The concentration of vosoritide in reconstituted 0.4 mg vial and 0.56 mg vial is 0.8 mg/mL. The concentration of vosoritide in reconstituted 1.2 mg vial is 2 mg/mL.]
3 kg | 0.096 mg | 0.12 mL | 0.4 mg
4 kg | 0.12 mg | 0.15 mL | 0.4 mg
5 kg | 0.16 mg | 0.2 mL | 0.4 mg
6 to 7 kg | 0.2 mg | 0.25 mL | 0.4 mg
8 to 11 kg | 0.24 mg | 0.3 mL | 0.4 mg
12 to 16 kg | 0.28 mg | 0.35 mL | 0.56 mg
17 to 21 kg | 0.32 mg | 0.4 mL | 0.56 mg
22 to 32 kg | 0.4 mg | 0.5 mL | 0.56 mg
33 to 43 kg | 0.5 mg | 0.25 mL | 1.2 mg
44 to 59 kg | 0.6 mg | 0.3 mL | 1.2 mg
60 to 89 kg | 0.7 mg | 0.35 mL | 1.2 mg
≥ 90 kg | 0.8 mg | 0.4 mL | 1.2 mg

Missed dose

If a dose of VOXZOGO is missed, it can be administered within 12 hours of the scheduled time of administration. Beyond 12 hours, skip the missed dose and administer the next daily dose according to the usual dosing schedule.

2.3 Growth Monitoring

Monitor and assess patient body weight, growth, and physical development regularly every 3 to 6 months. Adjust the dosage according to the patient's actual body weight [see Dosage and Administration (2.2)].

Permanently discontinue VOXZOGO upon confirmation of no further growth potential, indicated by closure of epiphyses.

2.4 Preparation and Administration

Reconstitute VOXZOGO before administration using the provided diluent syringe containing Sterile Water for Injection, USP (see Reconstitution Instructions below).

Caregivers may inject VOXZOGO subcutaneously after proper training by a healthcare professional on the preparation and administration of VOXZOGO [see Instructions for Use].

Reconstitution Instructions

- Select the correct VOXZOGO vial strength (co-packaged with prefilled syringe with Sterile Water for Injection diluent) based on the patient's actual body weight [see Dosage and Administration (2.2)].
- Remove VOXZOGO vial and prefilled diluent syringe from the refrigerator and allow the vial and prefilled diluent syringe to reach room temperature before reconstituting VOXZOGO.
- Attach the diluent needle provided with ancillary supplies to the diluent prefilled syringe.
- Inject the entire diluent prefilled syringe volume into the vial (see Table 2).
- Gently swirl the diluent in the vial until the white powder is completely dissolved. Do not shake.
- Parenteral drug products should be inspected visually for particulate matter and discoloration prior to administration whenever solution and container permit. Once reconstituted VOXZOGO is a clear, colorless to yellow liquid. The solution should not be used if discolored or cloudy, or if particles are present. The concentration of reconstituted solution is 0.8 mg/mL or 2.0 mg/mL (see Table 2).
- After reconstitution, VOXZOGO can be held in the vial at a room temperature 20°C to 25°C (68°F to 77°F) for a maximum of 3 hours.
- For administration, extract the required dose volume from the vial using the supplied administration syringe [see Dosage and Administration (2.2)].

Table 2: Dilution Requirements for VOXZOGO Prior to Administration
Vial Strength | Reconstitution Volume | Reconstituted Concentration
0.4 mg | 0.5 mL | 0.8 mg/mL
0.56 mg | 0.7 mL | 0.8 mg/mL
1.2 mg | 0.6 mL | 2 mg/mL

Discard any unused portion. Do not pool unused portions from the vials. Do not administer more than 1 dose from a vial. Do not mix with other medications.

Instructions for Subcutaneous Administration

See the Instructions for Use document for detailed, illustrated instructions.

- Ensure patients have had adequate food and fluid intake prior to VOXZOGO administration [see Dosage and Administration (2.1)]. Slowly withdraw the dosing volume of the reconstituted VOXZOGO solution from the single-dose vial into a syringe.
- Rotate sites for subcutaneous injections.
- The recommended injection sites for VOXZOGO are: the front middle of the thighs, the lower part of the abdomen at least 2 inches (5 centimeters) away from the navel, top of the buttocks or the back of the upper arms. The same injection area should not be used on two consecutive days. Do not inject VOXZOGO into sites that are red, swollen, or tender.

3 DOSAGE FORMS AND STRENGTHS

For Injection: 0.4 mg, 0.56 mg, or 1.2 mg of vosoritide as a white to yellow lyophilized powder in a single-dose vial for reconstitution.

4 CONTRAINDICATIONS

None

5 WARNINGS AND PRECAUTIONS

5.1 Risk of Low Blood Pressure

Transient decreases in blood pressure were observed in clinical studies of VOXZOGO. Subjects with significant cardiac or vascular disease and patients on anti-hypertensive medicinal products were excluded from participation in VOXZOGO clinical trials. To reduce the risk of a decrease in blood pressure and associated symptoms (dizziness, fatigue and/or nausea), instruct patients to be well hydrated and have adequate food intake prior to administration of VOXZOGO [see Dosage and Administration (2.1) and Adverse Reactions (6.1)].

6 ADVERSE REACTIONS

The following clinically significant adverse reactions are described elsewhere in the labeling:

- Risk of Low Blood Pressure [see Warnings and Precautions (5.1)]

6.1 Clinical Trials Experience

Because clinical trials are conducted under widely varying conditions, adverse reaction rates observed in the clinical trials of a drug cannot be directly compared to rates in the clinical trials of another drug and may not reflect the rates observed in practice.

Pediatric Patients 5 Years of Age and Older

VOXZOGO was studied in a 52-week, randomized, double-blind, placebo-controlled trial in 121 subjects with achondroplasia (Study 1) [see Clinical Studies (14)].

The subjects' ages ranged from 5.1 to 14.9 years with a mean of 8.7 years. Sixty four (53%) subjects were male and 57 (47%) were female. Overall, 86 (71%) subjects were White, 23 (19%) were Asian, 5 (4%) were Black or African American, and 7 (6%) were classified as "multiple" race. The demographic and baseline characteristics were balanced between treatment groups. The subjects received either VOXZOGO 15 mcg/kg, or placebo administered subcutaneously once daily.

Table 3 shows adverse reactions that occurred in ≥5% of patients treated with VOXZOGO and at a percentage greater than placebo.

Table 3: Adverse Reactions that Occurred in ≥5% of Patients Treated with VOXZOGO and at a Percentage Greater than Placebo in Study 1 [Includes adverse reactions occurring more frequently in the vosoritide arm and with a risk difference of ≥5% (i.e., difference of >2 subjects) between treatment arms]
Adverse Reaction | Placebo (N=61) n (%) | VOXZOGO (N=60) n (%)
Injection site erythema | 42 (69%) | 45 (75%)
Injection site swelling | 22 (36%) | 37 (62%)
Vomiting | 12 (20%) | 16 (27%)
Injection site urticaria | 6 (10%) | 15 (25%)
Arthralgia | 4 (7%) | 9 (15%)
Decreased blood pressure | 3 (5%) | 8 (13%)
Gastroenteritis [Includes the preferred terms: gastroenteritis and gastroenteritis, viral] | 5 (8%) | 8 (13%)
Diarrhea | 2 (3%) | 6 (10%)
Dizziness [Includes the preferred terms: dizziness, presyncope, procedural dizziness, vertigo] | 2 (3%) | 6 (10%)
Ear pain | 3 (5%) | 6 (10%)
Influenza | 3 (5%) | 6 (10%)
Fatigue [Includes the preferred terms: fatigue, lethargy, malaise] | 2 (3%) | 5 (8%)
Seasonal allergy | 1 (2%) | 4 (7%)
Dry skin | 0 | 3 (5%)
Abbreviations: N, total number of subjects in the treatment arm; n, number of subjects with the adverse reaction; %, percent of subjects with the adverse reaction.

Laboratory Abnormalities

Increase in Alkaline Phosphatase

More VOXZOGO-treated patients had an increase in alkaline phosphatase levels during the study compared to placebo (17% vs 7%).

Discussion of Selected Adverse Reactions

Decreased blood pressure

Eight (13%) of 60 subjects treated with VOXZOGO had a total of 11 events of transient decrease in blood pressure compared to 3 (5%) of 61 subjects on placebo, identified predominantly during periods of frequent monitoring at clinical visits after dosing over a 52-week treatment period. The median time to onset from injection was 31 (18 to 120) minutes with resolution within 31 (5 to 90) minutes in VOXZOGO-treated subjects. Two out of 60 (3%) VOXZOGO-treated subjects each had one symptomatic episode of decreased blood pressure with vomiting and/or dizziness compared to 0 of 61 (0%) subjects on placebo.

Injection site reactions

Injection site reactions occurred in 51 (85%) subjects receiving VOXZOGO and 50 (82%) subjects receiving placebo over a 52 week period of treatment. Injection site reactions included the preferred terms injection site erythema, injection site reaction, injection site swelling, injection site urticaria, injection site pain, injection site bruising, injection site pruritus, injection site hemorrhage, injection site discoloration, and injection site induration. Over a 52 week period, 51 (85%) of 60 subjects receiving VOXZOGO experienced a total of 6983 events of injection site reactions, while 50 (82%) of 61 subjects receiving placebo experienced a total of 1776 events of injections site reactions, representing 120.4 events per person/year exposure and 29.2 per person/year exposure, respectively. One injection site reaction event could have been associated with one or more injection site reaction symptoms (e.g., injection site swelling, injection site erythema, injection site urticaria, etc.). Two subjects in the VOXZOGO arm discontinued treatment due to adverse reactions of pain and anxiety with injections.

Pediatric Patients <5 Years

The safety of VOXZOGO in pediatric patients <5 years with achondroplasia was evaluated in a 52-week randomized, double blind, placebo-controlled study (Study 2). In this study, 64 patients from 4.4 months to <5 years of age were randomized to receive either a daily vosoritide dose with similar exposure to that characterized to be safe and effective in children with ACH aged ≥5 years old, or placebo. An additional 11 patients received open-label treatment as part of this study. Subjects received 30 mcg/kg while they were <2 years of age. The daily dose for subjects was adjusted to 15 mcg/kg immediately following their 2 year birthday. The most common adverse reactions (>10%) reported in pediatric patients <5 years were injection site reactions (86%) and rash (28%).

The overall safety profile of VOXZOGO in pediatric patients <5 years was similar to that seen in older pediatric patients.

6.2 Postmarketing Experience

The following adverse reactions have been identified during post approval use of VOXZOGO. Because these reactions are reported voluntarily from a population of uncertain size, it is not always possible to reliably estimate their frequency or establish a causal relationship to drug exposure.

Skin and Subcutaneous Tissue Disorders: hypertrichosis (includes the preferred terms: hair growth abnormal and hypertrichosis).

8 USE IN SPECIFIC POPULATIONS

8.1 Pregnancy

Risk Summary

There are no available data on vosoritide use in pregnant women to evaluate for a drug-associated risk of major birth defects, miscarriage, or adverse maternal or fetal outcomes. In animal reproduction studies, there was no evidence of embryo-fetal toxicity or congenital malformations when pregnant rats and rabbits were administered vosoritide subcutaneously at doses equivalent to 14-times and 200-times, respectively, the exposure at the maximum recommended human dose (MRHD) (see Data).

The estimated background risk of major birth defects for the indicated population is higher than the general population. The estimated background risk of miscarriage for the indicated population is unknown. All pregnancies have a background risk of birth defect, loss, or other adverse outcomes. In the U.S. general population, the estimated background risk of major birth defects and miscarriage in clinically recognized pregnancies is 2% to 4% and 15% to 20%, respectively.

Data

Animal Data

In an embryofetal developmental toxicity study in rats, vosoritide was administered at 90, 270, 540 mcg/kg once daily by subcutaneous injection during the period of major organogenesis from gestation day (GD) 6 – 17. There were no effects on maternal animals or on embryofetal development at the highest dose administered (14-times the exposure at the MRHD).

In an embryofetal developmental toxicity study in rabbits, vosoritide was administered at 45, 135, 240 mcg/kg once daily by subcutaneous injection during the period of major organogenesis (GD 7 – 19). No effects were observed in maternal animals or on embryofetal development at the highest dose administered (200-times the exposure at the MRHD).

In a pre- and postnatal toxicity study in rats, vosoritide was administered at 90, 270, and 540 mcg/kg once daily by subcutaneous injection during the period of major organogenesis and continuing to weaning (GD 6 through postpartum day 20). There were no effects on maternal animals, including maintenance of pregnancy, parturition, or care of offspring, and no effects were noted on offspring growth and development or ability to reproduce at the highest dose (14-times the exposure at the MRHD).

8.2 Lactation

Risk Summary

There is no information regarding the presence of vosoritide in human milk, the effects on the breastfed infant, or the effects on milk production. Vosoritide is present in rat milk. When a drug is present in animal milk, it is likely that the drug will be present in human milk. The developmental and health benefits of breastfeeding should be considered along with the mother's clinical need for VOXZOGO and any potential adverse effects on the breastfed child from VOXZOGO or from the underlying maternal condition.

8.4 Pediatric Use

The safety and effectiveness of VOXZOGO have been established in pediatric patients for the improvement in linear growth in patients with achondroplasia with open epiphyses.

Use of VOXZOGO for this indication is supported by evidence from an adequate and well-controlled study in 121 pediatric patients aged 5 to 15 years with achondroplasia, pharmacokinetic data in pediatric patients aged 4.5 months to 15 years, and additional safety data in pediatric patients aged 4.4 months to <5 years [see Adverse Reactions (6.1), Clinical Pharmacology (12.3), and Clinical Studies (14)].

8.6 Renal Impairment

The effect of renal impairment on the pharmacokinetics of VOXZOGO has not been evaluated. No dosage adjustment is needed for patients with eGFR ≥ 60 mL/min/1.73 m^2. VOXZOGO is not recommended for patients with eGFR < 60 mL/min/1.73 m^2.

11 DESCRIPTION

VOXZOGO contains vosoritide, a human C type natriuretic peptide (CNP) analog. Vosoritide is a 39 amino acid peptide. Its amino acid sequence includes the 37 C terminal amino acids of the human CNP53 sequence plus Pro Gly on the N terminus to convey resistance to neutral endopeptidase (NEP) degradation. Vosoritide is manufactured from Escherichia coli using recombinant DNA technology. Vosoritide has a chemical formula of C176H290N56O51S3 with a molecular weight of 4.1 kDa.

Vosoritide has the structural formula shown in Figure 1.

Figure 1

VOXZOGO (vosoritide) for injection, is a sterile, preservative-free white-to-yellow lyophilized powder, for subcutaneous administration after reconstitution with Sterile Water for Injection, USP.

VOXZOGO is provided as a single-dose vial containing 0.4 mg, 0.56 mg, or 1.2 mg of vosoritide per vial. A pre-filled syringe containing Sterile Water for Injection, USP for use as a diluent is also provided. The contents of each single dose vial are summarized by strength in Table 4. The product contains no preservative.

Table 4: Contents of VOXZOGO
Strength | Inactive Ingredients per Vial
VOXZOGO 0.4 mg | Citric acid monohydrate (0.14 mg), mannitol (7.5 mg), methionine (0.36 mg), polysorbate 80 (0.025 mg), sodium citrate dihydrate (0.54 mg) and trehalose dihydrate (29.01 mg). After reconstitution with 0.5 mL Sterile Water for Injection USP, the resulting concentration is 0.4 mg/0.5 mL of vosoritide and the nominal deliverable volume is 0.4 mL.
VOXZOGO 0.56 mg | Citric acid monohydrate (0.20 mg), mannitol (10.50 mg), methionine (0.51 mg), polysorbate 80 (0.035 mg), sodium citrate dihydrate (0.76 mg) and trehalose dihydrate (40.61 mg). After reconstitution with 0.7 mL Sterile Water for Injection USP, the resulting concentration is 0.56 mg/0.7 mL of vosoritide and the nominal deliverable volume is 0.6 mL.
VOXZOGO 1.2 mg | Citric acid monohydrate (0.17 mg), mannitol (9 mg), methionine (0.44 mg), polysorbate 80 (0.030 mg), sodium citrate dihydrate (0.65 mg) and trehalose dihydrate (34.81 mg). After reconstitution with 0.6 mL Sterile Water for Injection USP, the resulting concentration is 1.2 mg/0.6 mL of vosoritide and the nominal deliverable volume is 0.5 mL.
Trehalose dihydrate and D-Mannitol are used as isotonic agent. Citric acid monohydrate and sodium citrate dihydrate are used as buffering agent.

12 CLINICAL PHARMACOLOGY

12.1 Mechanism of Action

In patients with achondroplasia, endochondral bone growth is negatively regulated due to a gain of function mutation in fibroblast growth factor receptor 3 (FGFR3). Binding of vosoritide to natriuretic peptide receptor-B (NPR-B) antagonizes FGFR3 downstream signaling by inhibiting the extracellular signal-regulated kinases 1 and 2 (ERK1/2) in the mitogen-activated protein kinase (MAPK) pathway at the level of rapidly accelerating fibrosarcoma serine/threonine protein kinase (RAF-1). As a result, vosoritide, like CNP, acts as a positive regulator of endochondral bone growth as it promotes chondrocyte proliferation and differentiation.

In animal models with open growth plates, vosoritide administration resulted in the promotion of chondrocyte proliferation and differentiation that led to a widening of the growth plate and subsequent increase in skeletal growth. In the mouse models of FGFR3-related chondrodysplasia, a partial or complete normalization of the dwarfism phenotype was observed.

12.2 Pharmacodynamics

NPR-B Binding Activity Biomarker and Bone Metabolism Biomarker

An increase in urinary cyclic guanosine monophosphate (cGMP) concentrations from pre-dose baseline were observed within the first four hours post-dose, with a maximum level at 2 hours post-dose, after VOXZOGO administration to pediatric patients with achondroplasia.

Daily administration of VOXZOGO also led to the increase from baseline in serum collagen type X marker (CXM), an endochondral ossification biomarker and remains elevated beyond 24 months. In subjects aged 5 - 14 years old at screening, exposure-response analyses showed that vosoritide activity measured by urinary cGMP was near saturation at the dose of 15 mcg/kg once daily, while maximal increase in growth plate activity indicated by CXM was achieved at this dose.

Cardiac Electrophysiology

At the maximum approved recommended dose, VOXZOGO does not prolong the QT interval to any clinically relevant extent.

12.3 Pharmacokinetics

The area under the concentration-time curve (AUC) and peak concentration (Cmax) of vosoritide increased greater than proportionally following subcutaneous administration to pediatric subjects with achondroplasia in the dose range of 7.5 to 30.0 mcg/kg. The pharmacokinetics of vosoritide were evaluated in 58 subjects aged 5 to 13 years with achondroplasia who received subcutaneous injections of vosoritide 15 mcg/kg once daily for 52 weeks. The mean (± SD) Cmax and area under the concentration-time curve from time zero to the last measurable concentration (AUC0-t) observed across 52 weeks of treatment ranged from 4.71 (± 2.32) to 7.18 (± 9.65) ng/mL, and 161 (± 98.1) to 290 (± 235) ng-min/mL, respectively. No drug accumulation was observed following 15 mcg/kg once daily dosing. The exposure of vosoritide increased with the duration of treatment. The mean AUC0-t at week 52 increased approximately 20% compared to that at day 1.

Absorption

Absolute bioavailability for vosoritide following subcutaneous injection was not determined. Vosoritide was absorbed with a median Tmax of 15 minutes after dosing.

Distribution

The mean (± SD) apparent volume of distribution of vosoritide across 52 weeks of subcutaneous administration of VOXZOGO 15 mcg/kg once daily ranged from 2880 (± 2450) to 3020 (± 1980) mL/kg.

Elimination

The mean (± SD) apparent clearance of vosoritide across 52 weeks of subcutaneous administration of VOXZOGO 15 mcg/kg once daily ranged from 79.4 (± 53.0) to 104 (± 98.8) mL/min/kg. The mean (± SD) half-life ranged from 21.0 (± 4.7) to 27.9 (± 9.9) minutes.

Metabolism

The metabolism of vosoritide is expected to occur via catabolic pathways with degradation into small peptide fragments and amino acids.

Specific Populations

No clinically significant differences in the vosoritide pharmacokinetics were observed based on age (0.4 to 15 years), sex or race. The effect of hepatic or renal impairment on the pharmacokinetics of vosoritide is unknown.

Body weight

Population pharmacokinetic analyses indicated that body weight is a significant covariate for vosoritide clearance and volume of distribution. The apparent clearance and volume of distribution of vosoritide increased with increasing body weight in patients with achondroplasia (5 to 74.5 kg).

Drug Interaction Studies

In vitro assessment of drug-drug interactions

In vitro studies showed that vosoritide, at therapeutic concentrations, does not inhibit or induce Cytochrome P450 enzymes. Based on in vitro studies, vosoritide is considered unlikely to inhibit the human drug uptake or efflux transporters such as OAT1, OAT3, OCT1, OCT2, OATP1B1, OATP1B3, MATE1, MATE2-K, BCRP, P-gp, and BSEP at clinically relevant concentrations and therefore, no effect of vosoritide is anticipated on concomitantly administered drugs that are substrates of these transporters.

In vivo assessment of drug-drug interactions

No clinical studies evaluating the drug-drug interaction potential of vosoritide have been conducted.

12.6 Immunogenicity

The observed incidence of anti-drug antibodies is highly dependent on the sensitivity and specificity of the assay. Differences in assay methods preclude meaningful comparisons of the incidence of anti-drug antibodies in the studies described below with the incidence of anti-drug antibodies in other studies, including those of vosoritide.

Of 131 subjects aged 5 years and older who were treated with VOXZOGO 15 mcg/kg/day and evaluable for the presence of anti-drug antibodies (ADA) for up to 240 weeks, ADA were detected in 35% (46/131). The earliest time to ADA development was day 85. All ADA-positive subjects tested negative for anti-vosoritide neutralizing antibodies. There was no correlation between the number, duration, or severity of hypersensitivity adverse reactions or injection site reactions and ADA positivity or mean ADA titer. There was no association between ADA positivity or mean ADA titer and change from baseline in annual growth velocity (AGV) or height Z-score at month 12. There was no impact of serum ADA detected on the plasma PK measurements of vosoritide.

In subjects under 5 years of age, 33% (20/61) of vosoritide-treated subjects tested positive for ADA and all placebo-treated subjects tested negative for ADA for up to 44 months. The earliest time to ADA development was week 26. All of the ADA-positive subjects tested negative for neutralizing antibodies at all time points. There was no impact of ADA development on safety, efficacy or PK of vosoritide up to Month 12.

13 NONCLINICAL TOXICOLOGY

13.1 Carcinogenesis, Mutagenesis, Impairment of Fertility

Long term carcinogenicity studies and genotoxicity studies with vosoritide have not been performed.

In a fertility and reproductive study in male and female rats at doses up to 540 mcg/kg/day (15-times the exposure at the MRHD), vosoritide had no effect on mating performance, fertility, or litter characteristics.

14 CLINICAL STUDIES

14.1 Pediatric Patients 5 Years of Age and Older

The safety and effectiveness of VOXZOGO in patients with achondroplasia were assessed in one 52-week, multi-center, randomized, double-blind, placebo-controlled, phase 3 study - Study 1 (NCT03197766).

Study 1 was conducted in 121 subjects with genetically-confirmed achondroplasia, who were randomized to either VOXZOGO (N=60) or placebo (N=61). The dosage of VOXZOGO was 15 mcg/kg administered subcutaneously once daily. Baseline standing height, weight Z-score, body mass index (BMI) Z-score, and upper to lower body ratio were collected for at least 6 months prior to randomization. Subjects with limb-lengthening surgery in the prior 18 months or who planned to have limb-lengthening surgery during the study period were excluded. The study included a 52-week placebo-controlled treatment phase followed by an open-label treatment extension study period in which all subjects received VOXZOGO. The primary efficacy endpoint was the change from baseline in annualized growth velocity (AGV) at Week 52 compared with placebo.

The subjects' ages ranged from 5.1 to 14.9 years with a mean of 8.7 years. Sixty four (53%) subjects were male and 57 (47%) were female. Overall, 86 (71%) subjects were White, 23 (19%) were Asian, 5 (4%) were Black or African American, and 7 (6%) were classified as "multiple" race. The subjects had a mean baseline height standard deviation score (SDS) of -5.13.

Treatment with VOXZOGO for 52 weeks resulted in a treatment difference in the change from baseline in AGV of 1.57 cm/year after 52 weeks of treatment (Table 5).

Table 5: Annualized Growth Velocity (cm/year) at Week 52 in Subjects 5 Years of Age and Older with Achondroplasia - Study 1
 | Placebo (N=61 [All randomized subjects. Two patients in the VOXZOGO group discontinued from the study before Week 52. The values for these 2 patients were imputed assuming baseline growth rate for the period with missing data.]) | VOXZOGO 15 mcg/kg Daily (N=60)
Baseline mean (SD) [Baseline AGV was based on standing height at least 6 months prior to enrollment into the study.] | 4.06 (1.20) | 4.26 (1.53)
Change from baseline [LS means were estimated from the ANCOVA (analysis of covariance) model, which included treatment, stratum defined by sex and Tanner stage, baseline age, baseline AGV and baseline height Z-score.] | -0.17 | 1.40
Difference in change of VOXZOGO – Placebo (95% CI) | 1.57 (1.22, 1.93) [2-sided p-value <0.0001 for superiority.]
Abbreviations: AGV, annualized growth velocity; 95% CI, 95% confidence interval; LS, least-square; SD, standard deviation

The improvement in AGV in favor of VOXZOGO was consistent across all predefined subgroups analyzed including sex, age group, Tanner stage, baseline height Z-score, and baseline AGV.

Height Standard Deviation Score (SDS)

The LS mean change from baseline to Week 52 in height SDS was -0.02 in the placebo group and 0.26 in the VOXZOGO group. The difference in LS mean change from baseline was 0.28 (95% CI 0.17, 0.39; p<0.0001) in favor of VOXZOGO. The LS mean change from baseline to Week 52 in upper to lower body segment ratio was -0.02 in the placebo group and -0.03 in the VOXZOGO group. The difference in LS mean change from baseline was -0.01 (95% CI -0.05, 0.02; p=0.5).

Open-label extension

After the 52 week double blind, placebo-controlled, phase 3 study, Study 1, 58 subjects initially randomized to VOXZOGO enrolled into an open-label extension. Among the subjects who had 2 years of follow-up since randomization, the improvement in AGV was maintained.

16 HOW SUPPLIED/STORAGE AND HANDLING

How Supplied

VOXZOGO for injection is a white to yellow lyophilized powder for reconstitution and is provided as a co-pack which includes ten:

- Sterile, single-dose 2 mL glass vials containing VOXZOGO
- Diluent (Sterile Water for Injection, USP) in a single-dose prefilled syringe
- Diluent transfer needles (23 gauge)
- Single-dose administration syringes (30 gauge) both with needle retraction safety devices

Strength (mg) | Diluent (mL) | Co-pack NDC Number | Flip Cap Color
0.4 | 0.5 | NDC 68135-082-36 | White
0.56 | 0.7 | NDC 68135-119-66 | Magenta
1.2 | 0.6 | NDC 68135-181-93 | Grey

The following items to be obtained separately; alcohol aseptic wipes, gauze, bandages and sharps container.

Storage

Refrigerate VOXZOGO vials and prefilled diluent syringes at 2°C to 8°C (36°F to 46°F). Do not freeze.

VOXZOGO can be stored at room temperature 20°C to 25°C (68°F to 77°F); excursions permitted to 15°C to 30°C (59°F to 86°F) for 90 days. Do not return VOXZOGO to the refrigerator once stored at room temperature.

After reconstitution, VOXZOGO can be held in the vial at room temperature 20°C to 25°C (68°F to 77°F) for a maximum of 3 hours [see Dosage and Administration (2.4)].

Record the starting date of room-temperature storage clearly on the unopened product carton.

Do not use beyond expiration date on the label.

Store in the original package to protect from light.

Handling

Reconstituted VOXZOGO must be administered within 3 hours of reconstitution [see Dosage and Administration (2.4)].

17 PATIENT COUNSELING INFORMATION

Advise the patient and caregiver to read the FDA-approved patient labeling (Patient Information and Instructions for Use).

Preparation and Administration

Instruct caregivers on proper preparation and administration of VOXZOGO. Ensure caregivers have demonstrated the ability to perform a subcutaneous injection [see Dosage and Administration (2.4)].

Instruct caregivers in the technique of proper syringe and needle disposal, and advise them not to reuse these items. Instruct caregivers to dispose needles and syringes in a puncture-resistant container.

Risk of Low Blood Pressure

Inform caregivers and patients that VOXZOGO may lower blood pressure after administration. Instruct caregivers and patients that prior to VOXZOGO administration, the patient should have adequate food intake and within the hour prior to administration, the patient should drink approximately 8-10 ounces (240-300 mL) of fluid [see Dosage and Administration (2.1) and Warnings and Precautions (5.1)].

Manufactured for:
BioMarin Pharmaceutical Inc.
105 Digital Drive, Novato, CA 94949

PATIENT INFORMATION
VOXZOGO (vox zoeʹ goe)
(vosoritide)
for injection, for subcutaneous use

What is VOXZOGO?
VOXZOGO is a prescription medicine used to increase linear growth in children with achondroplasia with open bone growth plates (epiphyses).

Before you give your child VOXZOGO, tell your child's healthcare provider about all your child's medical conditions, including if they:

- have kidney problems.
- are pregnant or plan to become pregnant. It is not known if VOXZOGO will harm your child's unborn baby.
- are breastfeeding or plan to breastfeed. It is not known if VOXZOGO passes into your child's breast milk. Talk to your child's healthcare provider about the best way to feed your child's baby if your child takes VOXZOGO.

Tell your child's healthcare provider about all the medicines your child takes, including prescription and over-the-counter medicines, vitamins, and herbal supplements.
Know the medicines your child takes. Keep a list of them to show your child's healthcare provider and pharmacist when your child gets a new medicine.

How should I give VOXZOGO?

- See the detailed Instructions for Use that comes with this Patient Information leaflet for instructions about the right way to store, prepare, and give VOXZOGO injections at home.
- VOXZOGO is given as an injection under the skin (subcutaneous or SC). Inject VOXZOGO 1 time every day, at about the same time each day.
- If your child's healthcare provider decides a caregiver can give the injections of VOXZOGO at home, your child's caregiver should receive training on the right way to prepare and inject VOXZOGO. Do not try to inject VOXZOGO until you have been shown the right way by your child's healthcare provider or nurse.
- Your child's healthcare provider will tell you how often you should give VOXZOGO. If your child misses a dose of VOXZOGO, it can be given within 12 hours of the scheduled time of injection. If more than 12 hours have passed, do not give the missed dose. Give the next daily dose according to your child's usual schedule.
- Your child should eat a meal and drink about 8 to 10 ounces of fluid within 1 hour before injection.
- In case you are not sure when to inject VOXZOGO, call your child's healthcare provider or pharmacist. Do not give VOXZOGO more often than as directed by your child's healthcare provider.
- Your child's dose of VOXZOGO depends on his or her body weight. Your child's healthcare provider will tell you which strength of VOXZOGO to use and how much to give your child.
- Your child's healthcare provider will monitor your child's growth and instruct you on when your child should stop VOXZOGO if they determine that your child is no longer able to grow. Stop giving VOXZOGO to your child if instructed by your child's healthcare provider.

What are the possible side effects of VOXZOGO?
VOXZOGO may cause serious side effects, including:

- risk of low blood pressure. VOXZOGO may temporarily lower blood pressure in some people. To help reduce the risk of low blood pressure and its symptoms (dizziness, feeling tired, or nausea), your child should eat a meal and drink about 8 to 10 ounces of fluid within 1 hour before receiving VOXZOGO.

The most common side effects of VOXZOGO include:

- injection site reactions (redness, itching, swelling, bruising, rash, hives, pain)
- high levels of blood alkaline phosphatase (shown in blood tests)
- vomiting
- joint pain
- decreased blood pressure
- stomach ache

These are not all the possible side effects of VOXZOGO. For more information, ask your healthcare provider or pharmacist.
Call your doctor for medical advice about side effects. You may report side effects to FDA at 1-800-FDA-1088.

How should I store VOXZOGO?

- Store the VOXZOGO vial and prefilled diluent syringe in the refrigerator between 36°F to 46°F (2°C to 8°C).
- You may store VOXZOGO (before mixing) at room temperature between 68°F to 77°F (20°C to 25°C) for 90 days.
- Record the date you started storing VOXZOGO at room temperature on the carton to keep track of the 90 days.
- Do not return VOXZOGO to the refrigerator after it has been stored at room temperature. Throw VOXZOGO away if unused within 90 days of storing at room temperature.
- Do not use VOXZOGO past the expiration date.
- Do not freeze VOXZOGO.
- Store VOXZOGO out of direct sunlight.

Keep VOXZOGO and all medicines out of the reach of children.

General information about the safe and effective use of VOXZOGO.
Medicines are sometimes prescribed for purposes other than those listed in a Patient Information leaflet. Do not use VOXZOGO for a condition for which it was not prescribed.
Do not give VOXZOGO to other people, even if they have the same symptoms you have. It may harm them.
You can ask your pharmacist or healthcare provider for information about VOXZOGO that is written for health professionals.

What are the ingredients in VOXZOGO?
Active ingredient: vosoritide
Inactive ingredients: trehalose dihydrate, mannitol, sodium citrate dihydrate, methionine, citric acid monohydrate, and polysorbate 80
BioMarin Pharmaceutical Inc.
Novato, CA 94949
© BioMarin Pharmaceutical Inc. All rights reserved.
VOXZOGO is a registered trademark of BioMarin Pharmaceutical Inc.
For more information, go to www.VOXZOGO.com or call 1-877-695-8826.

This Patient Information has been approved by the U.S. Food and Drug Administration.

Revised: 10/2023

INSTRUCTIONS FOR USE VOXZOGO™ [Vox zoeʹ goe] (vosoritide) for injection, for subcutaneous use Single-Use

This Instructions for Use contains information for caregivers on how to inject VOXZOGO.

Read this Instructions for Use before you start using VOXZOGO and each time you get a refill. There may be new information. This information does not take the place of talking to your child's healthcare provider about your child's medical condition and their treatment. Before you use VOXZOGO for the first time, make sure your child's healthcare provider shows you the right way to use it. Contact your child's healthcare provider if you or your child have any questions.

Important Information You Need to Know Before Injecting VOXZOGO

- Wash your hands with soap and water.
- Do not drop VOXZOGO or put opened items down on surfaces that are not clean.
- VOXZOGO is available in more than 1 strength. Make sure the strength matches your prescription strength. Do not open packaging until ready to use.
- Take the VOXZOGO vial and prefilled diluent syringe out of the refrigerator and allow them to reach room temperature before mixing.
- Inspect the vial and supplies for any signs of damage or contamination. Do not use if damaged or contaminated.
- Check the expiration date. The expiration date can be found on the carton, vial and prefilled diluent syringe. Do not use if expired.
- Your child should eat a meal and drink a glass (about 8 to 10 ounces) of fluid (such as water, milk, or juice) within 1 hour before injection.
- VOXZOGO should be given at about the same time every day.
- Do not mix VOXZOGO with other medicines.
- After mixing the VOXZOGO, use it right away. Do not use the mixed VOXZOGO if it has been sitting at room temperature for more than 3 hours. Throw it away (dispose of) in a sharps container. See step 18 and "How to Throw Away (Dispose of) VOXZOGO" for more information.
- Do not reuse any of the supplies. After the injection, throw away (dispose of) the used vial even if there is VOXZOGO remaining. See step 18 and "How to Throw Away (Dispose of) VOXZOGO" for more information.

How to Store VOXZOGO

- Store the VOXZOGO vial and prefilled diluent syringe in the refrigerator between 36°F to 46°F (2°C to 8°C).
- You may store VOXZOGO (before mixing) at room temperature between 68°F to 77°F (20°C to 25°C) for 90 days. Record the date you started storing VOXZOGO at room temperature on the carton to keep track of the 90 days. Do not return VOXZOGO to the refrigerator after it has been stored at room temperature. Throw VOXZOGO away if unused within 90 days of storing at room temperature.
- Do not freeze VOXZOGO.
- Store VOXZOGO out of direct sunlight.

Keep VOXZOGO and all other medicines out of the reach of children.

Supplies Needed to Inject VOXZOGO

Gather all of these supplies on a clean, flat surface before injecting.

Items supplied

Items not supplied
If you do not have these items, ask your pharmacist.

VOXZOGO

Preparing VOXZOGO for Injection

▶ Step 1
On a clean flat surface, flip off the vial cap and wipe the top with an alcohol pad.

▶ Step 2
Gently bend to snap off the cap from the prefilled diluent syringe.

▶ Step 3
Twist the diluent needle onto the prefilled diluent syringe until you can no longer twist it. Do not use the prefilled diluent syringe to give the injection.

▶ Step 4
Pull off the needle cap and insert the needle through the middle of the vial stopper. Slowly push the plunger rod down to inject all of the liquid.

▶ Step 5
Remove the needle from the vial, then press the blue tab for the needle to pull back (retract). Throw away the needle and syringe in a sharps container. See step 18 and "How to Throw Away (Dispose of) VOXZOGO." Do not use the prefilled diluent syringe to give the injection.

▶ Step 6
Gently swirl the vial until the powder has completely dissolved and the solution is clear. Do not shake.

▶ Step 7
Take the injection syringe out of the carton. Pull off the needle cap from the injection syringe and insert the needle straight through the middle of the vial stopper. Be careful not to bend the needle.

▶ Step 8
Carefully hold the vial and syringe and turn the vial upside down with the needle still inserted. The vial should be on top. Be careful not to bend the needle.

▶ Step 9
Keep the needle tip in the medicine and slowly pull the plunger rod back to draw up the prescribed dose in the syringe. Check the prescription label for how much to draw up.

▶ Step 10
Remove large air bubbles in the syringe by gently tapping the syringe. Then push the bubbles back into the vial.

▶ Step 11
Repeat steps 9 and 10 until you have the correct prescribed dose in the syringe and no large bubbles.

▶ Step 12
Make sure you have the prescribed dose in the syringe, then remove the vial and prepare to give the dose.

Select and Prepare Injection Site

▶ Step 13

▶ Step 14

VOXZOGO should be injected into the fatty layer under the skin (subcutaneous) only.
Do not inject into the same site 2 times in a row.

Wipe the injection site with an alcohol pad and let the skin air dry.

Giving VOXZOGO Injection

▶ Step 15

▶ Step 16

After wiping the site with an alcohol pad, pinch the skin up around the selected injection site.

Quickly insert the needle all the way into the skin at a 45-degree angle.

▶ Step 17
Release the pinch and slowly push the plunger rod all the way down.

Continue pressing the plunger rod until the needle retracts into the syringe.

▶ Step 18
Throw away the used vial, syringes and needles in a sharps container. See "How to Throw Away (Dispose of) VOXZOGO" for more information.

How to Throw Away (Dispose of) VOXZOGO

Put your used or expired vials, needles and syringes in a FDA-cleared sharps disposal container right away after use. Do not throw away (dispose of) the vials, loose needles and syringes in your household trash.

If you do not have a FDA-cleared sharps disposal container, you may use a household container that:

- is made of a heavy-duty plastic,
- can be closed with a tight-fitting, puncture-resistant lid without sharps being able to come out,
- is upright and stable during use,
- is leak-resistant, and
- is properly labeled to warn of hazardous waste inside the container.

When your sharps disposal container is almost full, you will need to follow your community guidelines for the right way to dispose of your sharps disposal container. There may be local or state laws about how you should throw away used needles and syringes. For more information about safe sharps disposal, and for specific information about sharps disposal in the state that you live in, go to the FDA's website at: http://www.fda.gov/safesharpsdisposal

Do not dispose of your used sharps disposal container in your household trash unless your community guidelines permit this. Do not recycle your used sharps disposal container.

After the Injection

- Inspect the injection site. If a small amount of bleeding occurs from the injection site, gently press a gauze pad on it for a few seconds or apply a bandage. Do not rub the injection site.
- Monitor for signs of low blood pressure, such as dizziness, tiredness, and nausea. If your child experiences these symptoms you should call your child's healthcare provider, then get your child to lay back with legs raised.

For Help or More Information

- Call your healthcare provider
- Call BioMarin at 1-800-123-4567
- Visit www.VOXZOGO.com

Manufactured for:
BioMarin Pharmaceutical Inc.,
Novato, CA 94949

REP-5233-C10

This Instructions for Use has been approved by the U.S. Food and Drug Administration.
Approved: November 2021

PRINCIPAL DISPLAY PANEL - Kit Carton - 68135-082

NDC 68135-082-36

Rx Only

VOXZOGO™
(vosoritide) for injection

0.4 mg per vial

For Subcutaneous Use Only

This carton contains:
- Ten single-dose vials of Voxzogo
- Ten disposable prefilled syringes
containing 0.5 mL diluent (Sterile
Water for Injection, USP) for Voxzogo
- Ten sterile, disposable needles for
prefilled diluent syringes
- Ten sterile disposable 1 mL syringes
with needles for dosing
- One Prescribing Information
- One Instructions for Use
- One Patient Information

Must be reconstituted
with diluent provided

BiOMARIN®

PRINCIPAL DISPLAY PANEL - 0.4 mg Vial Label

VOXZOGO™
(vosoritide) for injection

0.4 mg per vial

Reconstitute Prior to Use

For Subcutaneous Use Only

Single-dose vial
Rx Only

LOT:

EXP:

PRINCIPAL DISPLAY PANEL - 0.5 mL Syringe Label

NDC 68135-070-12
Rx Only

Diluent
For VOXZOGO™ for Injection

0.5 mL

For drug diluent use only-
reconstitute as directed

Single-dose

No preservative

Distributed by: BioMarin

MLC7246001

LOT:

EXP:

10008821-02

PRINCIPAL DISPLAY PANEL - Kit Carton - 68135-119

NDC 68135-119-66

Rx Only

VOXZOGO™
(vosoritide) for injection

0.56 mg per vial

For Subcutaneous Use Only

This carton contains:
- Ten single-dose vials of Voxzogo
- Ten disposable prefilled syringes
containing 0.7 mL diluent (Sterile
Water for Injection, USP) for Voxzogo
- Ten sterile, disposable needles for
prefilled diluent syringes
- Ten sterile disposable 1 mL syringes
with needles for dosing
- One Prescribing Information
- One Instructions for Use
- One Patient Information

Must be reconstituted
with diluent provided

BiOMARIN®

PRINCIPAL DISPLAY PANEL - 0.56 mg Vial Label

VOXZOGO™
(vosoritide) for injection

0.56 mg per vial

Reconstitute Prior to Use

For Subcutaneous Use Only

Single-dose vial
Rx Only

LOT:

EXP:

PRINCIPAL DISPLAY PANEL - 0.7 mL Syringe Label

NDC 68135-102-43
Rx Only

Diluent
For VOXZOGO™ for Injection

0.7 mL

For drug diluent use only-
reconstitute as directed

Single-dose

No preservative

Distributed by: BioMarin

MLC7246001

LOT:

EXP:

10008843-02

PRINCIPAL DISPLAY PANEL - Kit Carton - 68135-181

NDC 68135-181-93

Rx Only

VOXZOGO™
(vosoritide) for injection

1.2 mg per vial

For Subcutaneous Use Only

This carton contains:
- Ten single-dose vials of Voxzogo
- Ten disposable prefilled syringes
containing 0.6 mL diluent (Sterile
Water for Injection, USP) for Voxzogo
- Ten sterile, disposable needles for
prefilled diluent syringes
- Ten sterile disposable 1 mL syringes
with needles for dosing
- One Prescribing Information
- One Instructions for Use
- One Patient Information

Must be reconstituted
with diluent provided

BiOMARIN®

PRINCIPAL DISPLAY PANEL - 1.2 mg Vial Label

VOXZOGO™
(vosoritide) for injection

1.2 mg per vial

Reconstitute Prior to Use

For Subcutaneous Use Only

Single-dose vial
Rx Only

LOT:

EXP:

PRINCIPAL DISPLAY PANEL - 0.6 mL Syringe Label

NDC 68135-158-17
Rx Only

Diluent
For VOXZOGO™ for Injection

0.6 mL

For drug diluent use only-
reconstitute as directed

Single-dose

No preservative

Distributed by: BioMarin

MLC7246201

LOT:

EXP:

10008822-02